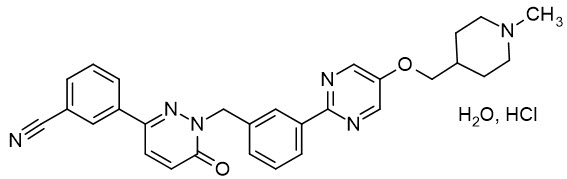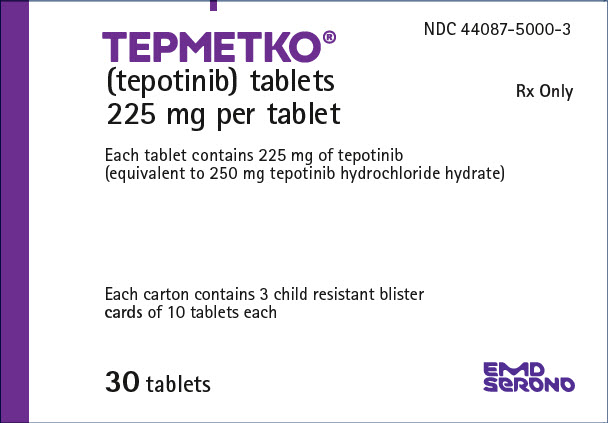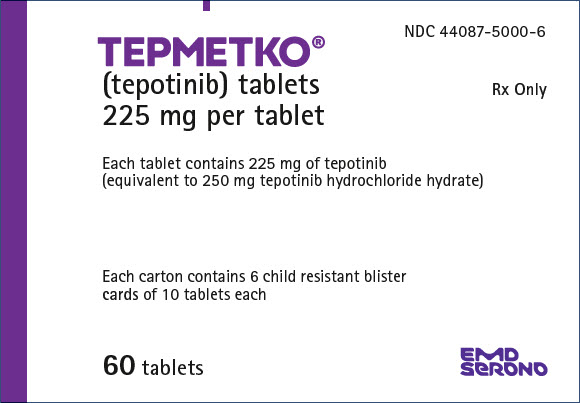 DRUG LABEL: TEPMETKO
NDC: 44087-5000 | Form: TABLET
Manufacturer: EMD Serono, Inc.
Category: prescription | Type: HUMAN PRESCRIPTION DRUG LABEL
Date: 20250417

ACTIVE INGREDIENTS: Tepotinib Hydrochloride 225 mg/1 1
INACTIVE INGREDIENTS: Mannitol; Microcrystalline Cellulose; Crospovidone, Unspecified; Magnesium stearate; Silicon Dioxide; Hypromellose, Unspecified; Lactose monohydrate; Polyethylene Glycol, Unspecified; Triacetin; Ferric oxide red; Titanium dioxide

HIGHLIGHTS OF PRESCRIBING INFORMATION

These highlights do not include all the information needed to use TEPMETKO safely and effectively. See full prescribing information for TEPMETKO.
TEPMETKO® (tepotinib) tablets, for oral use
Initial U.S. Approval: 2021

RECENT MAJOR CHANGES

Indication and Usage (1) | 02/2024
Dosage and Administration (2.3, 2.4) | 02/2024
Warnings and Precautions (5.3) | 02/2024

1 INDICATIONS AND USAGE

TEPMETKO is a kinase inhibitor indicated for the treatment of adult patients with metastatic non-small cell lung cancer (NSCLC) harboring mesenchymal-epithelial transition (MET) exon 14 skipping alterations. (1)

2 DOSAGE AND ADMINISTRATION

- Select patients for treatment with TEPMETKO on the presence of METex14 skipping. (2.1, 14)
- Recommended dosage: 450 mg orally once daily with food until disease progression or unacceptable toxicity. (2.2)

3 DOSAGE FORMS AND STRENGTHS

Tablets: 225 mg. (3)

4 CONTRAINDICATIONS

None. (4)

5 WARNINGS AND PRECAUTIONS

- Interstitial Lung Disease (ILD)/Pneumonitis: Immediately withhold TEPMETKO in patients with suspected ILD/pneumonitis. Permanently discontinue TEPMETKO in patients diagnosed with ILD/pneumonitis of any severity. (2.4, 5.1)
- Hepatotoxicity: Monitor liver function tests. Withhold, dose reduce, or permanently discontinue TEPMETKO based on severity. (5.2)
- Pancreatic Toxicity: Monitor amylase and lipase. Withhold, dose reduce, or permanently discontinue TEPMETKO based on severity. (5.3)
- Embryo-fetal toxicity: TEPMETKO can cause fetal harm. Advise of potential risk to a fetus and use of effective contraception. (5.4, 8.1, 8.3)

6 ADVERSE REACTIONS

Most common adverse reactions (≥ 20%) were edema, nausea, fatigue, musculoskeletal pain, diarrhea, dyspnea, decreased appetite, and rash. The most common Grade 3 to 4 laboratory abnormalities (≥ 2%) were decreased lymphocytes, decreased albumin, decreased sodium, increased gamma-glutamyltransferase, increased amylase, increased lipase, increased ALT, increased AST, and decreased hemoglobin. (6.1)

To report SUSPECTED ADVERSE REACTIONS, contact EMD Serono at 1-800-283-8088 ext. 5563 or FDA at 1-800-FDA-1088 or www.fda.gov/medwatch.

7 DRUG INTERACTIONS

- Certain P-gp substrates: Avoid coadministration of TEPMETKO with P-gp substrates where minimal concentration changes may lead to serious or life-threatening toxicities. (7.1)

8 USE IN SPECIFIC POPULATIONS

Lactation: Advise not to breastfeed. (8.2)

FULL PRESCRIBING INFORMATION

1 INDICATIONS AND USAGE

TEPMETKO is indicated for the treatment of adult patients with metastatic non-small cell lung cancer (NSCLC) harboring mesenchymal-epithelial transition (MET) exon 14 skipping alterations.

2 DOSAGE AND ADMINISTRATION

2.1 Patient Selection for METex14 Skipping Alterations

Select patients for treatment with TEPMETKO based on the presence of MET exon 14 skipping alterations in plasma or tumor specimens. Testing for the presence of MET exon 14 skipping alterations in plasma specimens is recommended only in patients for whom a tumor biopsy cannot be obtained. If an alteration is not detected in a plasma specimen, re-evaluate the feasibility of biopsy for tumor tissue testing. An FDA-approved test for detection of MET exon 14 skipping alterations in NSCLC for selecting patients for treatment with TEPMETKO is not available.

2.2 Recommended Dosage

The recommended dosage of TEPMETKO is 450 mg orally once daily with food [see Clinical Pharmacology (12.3)] until disease progression or unacceptable toxicity.

Instruct patients to take their dose of TEPMETKO at approximately the same time every day and to swallow tablets whole. Do not chew, crush or split tablets. Patients who have difficulty swallowing solids can disperse tablets in water [see Dosage and Administration (2.3)].

Advise patients not to make up a missed dose within 8 hours of the next scheduled dose.

If vomiting occurs after taking a dose of TEPMETKO, advise patients to take the next dose at the scheduled time.

2.3 Administration to Patients Who Have Difficulty Swallowing Solids

Place TEPMETKO tablet(s) in a glass containing 30 mL (1 ounce) of non-carbonated water. No other liquids should be used or added. Stir, without crushing, until the tablet(s) is dispersed into small pieces (tablets will not completely dissolve) and drink immediately or within 1 hour. Swallow the tablet dispersion. Do not chew pieces of the tablet. Rinse the glass with an additional 30 mL and drink immediately ensuring no residue remains in the glass and the full dose is administered.

If an administration via a naso-gastric tube (with at least 8 French gauge) is required, disperse the tablet(s) in 30 mL of non-carbonated water as described above. Administer the 30 mL of liquid immediately or within 1 hour as per naso-gastric tube manufacturer's instructions. Immediately rinse twice with 30 mL each time to ensure that no residue remains in the glass or syringe and the full dose is administered.

2.4 Dose Modifications for Adverse Reactions

The recommended dose reduction of TEPMETKO for the management of adverse reactions is 225 mg orally once daily.

Permanently discontinue TEPMETKO in patients who are unable to tolerate 225 mg orally once daily.

The recommended dosage modifications of TEPMETKO for adverse reactions are provided in Table 1.

Table 1: Recommended TEPMETKO Dosage Modifications for Adverse Reactions
Adverse Reaction | Severity [Severity as defined by National Cancer Institute Common Terminology Criteria for Adverse Events (NCI CTCAE) Version 5.] | Dose Modification
Interstitial Lung Disease (ILD)/Pneumonitis [see Warnings and Precautions (5.1)] | Any Grade | Withhold TEPMETKO if ILD is suspected. Permanently discontinue TEPMETKO if ILD is confirmed.
Increased ALT and/or AST without increased total bilirubin [see Warnings and Precautions (5.2)] | Grade 3 | Withhold TEPMETKO until recovery to baseline ALT/AST. If recovered to baseline within 7 days, then resume TEPMETKO at the same dose; otherwise resume TEPMETKO at a reduced dose.
Increased ALT and/or AST without increased total bilirubin [see Warnings and Precautions (5.2)] | Grade 4 | Permanently discontinue TEPMETKO.
Increased ALT and/or AST with increased total bilirubin in the absence of cholestasis or hemolysis [see Warnings and Precautions (5.2)] | ALT and/or AST greater than 3 times ULN with total bilirubin greater than 2 times ULN | Permanently discontinue TEPMETKO.
Increased total bilirubin without concurrent increased ALT and/or AST [see Warnings and Precautions (5.2)] | Grade 3 | Withhold TEPMETKO until recovery to baseline bilirubin. If recovered to baseline within 7 days, then resume TEPMETKO at a reduced dose; otherwise permanently discontinue.
Increased total bilirubin without concurrent increased ALT and/or AST [see Warnings and Precautions (5.2)] | Grade 4 | Permanently discontinue TEPMETKO.
Increased lipase or amylase [see Warnings and Precautions (5.3)] | Grade 3 | Withhold TEPMETKO until ≤ Grade 2 or baseline. If recovered to baseline or ≤ Grade 2 within 14 days, resume TEPMETKO at a reduced dose; otherwise permanently discontinue TEPMETKO.
Increased lipase or amylase [see Warnings and Precautions (5.3)] | Grade 4 | Permanently discontinue TEPMETKO.
Pancreatitis [see Warnings and Precautions (5.3)] | Grade 3 or 4 | Permanently discontinue TEPMETKO.
Other adverse reactions [see Adverse Reactions (6.1)] | Grade 2 | Maintain dose level. If intolerable, consider withholding TEPMETKO until resolved, then resume TEPMETKO at a reduced dose.
Other adverse reactions [see Adverse Reactions (6.1)] | Grade 3 | Withhold TEPMETKO until resolved, then resume TEPMETKO at a reduced dose.
Other adverse reactions [see Adverse Reactions (6.1)] | Grade 4 | Permanently discontinue TEPMETKO.

3 DOSAGE FORMS AND STRENGTHS

Tablets: 225 mg, white-pink, oval, biconvex film-coated tablets with embossment "M" on one side and plain on the other side.

4 CONTRAINDICATIONS

None.

5 WARNINGS AND PRECAUTIONS

5.1 Interstitial Lung Disease (ILD)/Pneumonitis

ILD/pneumonitis, which can be fatal, occurred in patients treated with TEPMETKO [see Adverse Reactions (6.1)]. ILD/pneumonitis occurred in 2% patients treated with TEPMETKO, with one patient experiencing a Grade 3 or higher event; this event resulted in death. Five patients (1%) discontinued TEPMETKO due to ILD/pneumonitis.

Monitor patients for new or worsening pulmonary symptoms indicative of ILD/pneumonitis (e.g., dyspnea, cough, fever). Immediately withhold TEPMETKO in patients with suspected ILD/pneumonitis and permanently discontinue if no other potential causes of ILD/pneumonitis are identified [see Dosage and Administration (2.4)].

5.2 Hepatotoxicity

Hepatotoxicity occurred in patients treated with TEPMETKO [see Adverse Reactions (6.1)]. Increased alanine aminotransferase (ALT)/increased aspartate aminotransferase (AST) occurred in 18% of patients treated with TEPMETKO. Grade 3 or 4 increased ALT/AST occurred in 4.7% of patients. A fatal adverse reaction of hepatic failure occurred in one patient (0.2%). Four patients (0.8%) discontinued TEPMETKO due to increased ALT/AST. The median time-to-onset of Grade 3 or higher increased ALT/AST was 47 days (range 1 to 262).

Monitor liver function tests (including ALT, AST, and total bilirubin) prior to the start of TEPMETKO, every 2 weeks during the first 3 months of treatment, then once a month or as clinically indicated, with more frequent testing in patients who develop increased transaminases or bilirubin. Based on the severity of the adverse reaction, withhold, dose reduce, or permanently discontinue TEPMETKO [see Dosage and Administration (2.4)].

5.3 Pancreatic Toxicity

Elevations in amylase and lipase levels occurred in patients treated with TEPMETKO [see Adverse Reactions (6.1)]. Increased amylase and/or lipase occurred in 13% of patients treated with TEPMETKO. Grade 3 and 4 increased amylase and/or lipase occurred in 5% and 1.2% of patients, respectively. Monitor amylase and lipase at baseline and regularly during treatment with TEPMETKO. Based on the severity of the adverse drug reaction, temporarily withhold, dose reduce, or permanently discontinue TEPMETKO [see Dosage and Administration (2.4)].

5.4 Embryo-Fetal Toxicity

Based on findings in animal studies and its mechanism of action TEPMETKO can cause fetal harm when administered to a pregnant woman. Oral administration of tepotinib to pregnant rabbits during the period of organogenesis resulted in malformations (teratogenicity) and anomalies at exposures less than the human exposure based on area under the curve (AUC) at the 450 mg daily clinical dose. Advise pregnant women of the potential risk to a fetus. Advise females of reproductive potential or males with female partners of reproductive potential to use effective contraception during treatment with TEPMETKO and for one week after the last dose. [See Use in Specific Populations (8.1, 8.3)]

6 ADVERSE REACTIONS

The following adverse reactions are described in greater detail elsewhere in the labeling:

- Interstitial Lung Disease/Pneumonitis [see Warnings and Precautions (5.1)]
- Hepatotoxicity [see Warnings and Precautions (5.2)]
- Pancreatic Toxicity [see Warnings and Precautions (5.3)]

6.1 Clinical Trials Experience

Because clinical trials are conducted under widely varying conditions, adverse reaction rates observed in the clinical trials of a drug cannot be directly compared to rates in the clinical trials of another drug and may not reflect the rates observed in practice.

The pooled safety population described in the WARNINGS AND PRECAUTIONS reflect exposure to TEPMETKO in 506 patients with solid tumors enrolled in five open-label, single-arm studies receiving TEPMETKO as single agent at a dose of 450 mg once daily. This included 313 patients with NSCLC positive for METex14 skipping alterations, who received TEPMETKO in VISION. Among 506 patients who received TEPMETKO, 44% were exposed for 6 months or longer, and 22% were exposed for more than one year.

The data described below reflect exposure to TEPMETKO 450 mg once daily in 313 patients with metastatic non-small cell lung cancer (NSCLC) with METex14 skipping alterations in VISION [see Clinical Studies (14)].

Serious adverse reactions occurred in 51% of patients who received TEPMETKO. Serious adverse reactions in > 2% of patients included pleural effusion (6%), pneumonia (6%), edema (5%), general health deterioration (3.8%), dyspnea (3.5%), musculoskeletal pain (2.9%), and pulmonary embolism (2.2%). Fatal adverse reactions occurred in 1.9% of patients who received TEPMETKO, including pneumonitis (0.3%), hepatic failure (0.3%), dyspnea from fluid overload (0.3%), pneumonia (0.3%), sepsis (0.3%), and death of unknown cause (0.3%).

Permanent discontinuation due to an adverse reaction occurred in 25% of patients who received TEPMETKO. The most frequent adverse reactions (> 1%) leading to permanent discontinuations of TEPMETKO were edema (8%), pleural effusion (1.6%), and general health deterioration (1.6%).

Dosage interruptions due to an adverse reaction occurred in 53% of patients who received TEPMETKO. Adverse reactions which required dosage interruption in > 2% of patients who received TEPMETKO included edema (28%), increased blood creatinine (6%), pleural effusion (3.5%), nausea (3.2%), increased ALT (2.9%), pneumonia (2.6%), decreased appetite (2.2%), and dyspnea (2.2%).

Dose reductions due to an adverse reaction occurred in 36% of patients who received TEPMETKO. Adverse reactions which required dose reductions in > 2% of patients who received TEPMETKO included edema (22%), increased blood creatinine (2.9%), fatigue (2.2%), and pleural effusion (2.2%).

The most common adverse reactions (≥ 20%) in patients who received TEPMETKO were edema, nausea, fatigue, musculoskeletal pain, diarrhea, dyspnea, decreased appetite, and rash. The most common Grade 3 to 4 laboratory abnormalities (≥ 2%) were decreased lymphocytes, decreased albumin, decreased sodium, increased gamma-glutamyltransferase, increased amylase, increased lipase, increased ALT, increased AST, and decreased hemoglobin.

Table 2 summarizes the adverse reactions in VISION.

Table 2: Adverse Reactions in ≥ 10% of Patients with NSCLC with METex14 Skipping Alterations Who Received TEPMETKO in VISION
Adverse Reactions | TEPMETKO (N=313)
Adverse Reactions | All Grades [Severity as defined by National Cancer Institute Common Terminology Criteria for Adverse Events (NCI CTCAE) version 4.03.] (%) | Grades 3 to 4 (%)
General disorders and administration-site conditions
Edema [Edema includes eye edema, face edema, generalized edema, localized edema, edema, genital edema, peripheral edema, peripheral swelling, periorbital edema, and scrotal edema.] | 81 | 16
Fatigue [Fatigue includes asthenia and fatigue.] | 30 | 1.9
Gastrointestinal disorders
Nausea | 31 | 1.3
Diarrhea | 29 | 0.6
Abdominal pain [Abdominal pain includes abdominal discomfort, abdominal pain, abdominal pain lower, abdominal pain upper, gastrointestinal pain, and hepatic pain.] | 19 | 0.6
Constipation | 19 | 0.3
Vomiting [Vomiting includes retching and vomiting.] | 15 | 1
Musculoskeletal and Connective Tissue Disorders
Musculoskeletal pain [Musculoskeletal pain includes arthralgia, arthritis, back pain, bone pain, musculoskeletal chest pain, musculoskeletal pain, myalgia, non-cardiac chest pain, pain in extremity, and spinal pain.] | 30 | 3.2
Respiratory, thoracic, and mediastinal disorders
Dyspnea [Dyspnea includes dyspnea, dyspnea at rest, and dyspnea exertional.] | 24 | 2.6
Cough [Cough includes cough, and productive cough.] | 18 | 0.3
Pleural effusion | 14 | 4.2
Metabolism and nutrition disorders
Decreased appetite | 21 | 1.9
Skin and Subcutaneous Tissue Disorders
Rash [Rash includes rash, palmar-plantar erythrodysesthesia syndrome, rash maculo-papular, eczema, exfoliative rash, rash erythematous, rash pustular, skin exfoliation, dermatitis acneiform, drug eruption, dermatitis, rash pruritic, dermatitis bullous, toxic skin eruption.] | 21 | 1.3
Infections and Infestations
Pneumonia [Pneumonia includes pneumonia, pneumonia aspiration, and pneumonia bacterial.] | 12 | 3.8

Clinically relevant adverse reactions in < 10% of patients who received TEPMETKO included ILD/pneumonitis, fever, dizziness, pruritus, and headache.

Table 3 summarizes the laboratory abnormalities observed in VISION.

Table 3: Select Laboratory Abnormalities (≥ 20%) That Worsened from Baseline in Patients Who Received TEPMETKO in VISION
Laboratory Abnormalities | TEPMETKO [The denominator used to calculate the rate varied from 268 to 309 based on the number of patients with a baseline value and at least one post-treatment value.]
Laboratory Abnormalities | Grades 1 to 4 [Severity as defined by National Cancer Institute Common Terminology Criteria for Adverse Events (NCI CTCAE) version 4.03.] (%) | Grades 3 to 4 (%)
Chemistry
Decreased albumin | 81 | 9
Increased creatinine | 60 | 1
Increased alkaline phosphatase aminotransferase | 52 | 1.6
Increased alanine aminotransferase | 50 | 4.9
Increased aspartate aminotransferase | 40 | 3.6
Decreased sodium | 36 | 9
Increased gamma-glutamyltransferase | 29 | 6
Increased potassium | 26 | 1.9
Increased amylase | 25 | 5
Increased lipase | 21 | 5
Hematology
Decreased lymphocytes | 57 | 15
Decreased hemoglobin | 31 | 3.6
Decreased leukocytes | 25 | 1.9
Decreased platelets | 24 | 0.6

Increased Creatinine

A median increase in serum creatinine of 30% was observed 21 days after initiation of treatment with TEPMETKO. The serum creatinine increases persisted throughout treatment and were reversible upon treatment completion.

7 DRUG INTERACTIONS

7.1 Effects of TEPMETKO on Other Drugs

Certain P-gp Substrates

Tepotinib is a P-gp inhibitor. Concomitant use of TEPMETKO increases the concentration of P-gp substrates [see Clinical Pharmacology (12.3)], which may increase the incidence and severity of adverse reactions of these substrates. Avoid concomitant use of TEPMETKO with certain P-gp substrates where minimal concentration changes may lead to serious or life-threatening toxicities. If concomitant use is unavoidable, reduce the P-gp substrate dosage if recommended in its approved product labeling.

8 USE IN SPECIFIC POPULATIONS

8.1 Pregnancy

Risk Summary

Based on findings in animal studies and the mechanism of action [see Clinical Pharmacology (12.1)], TEPMETKO can cause fetal harm when administered to a pregnant woman. There are no available data on the use of TEPMETKO in pregnant women. Oral administration of tepotinib to pregnant rabbits during the period of organogenesis resulted in malformations (teratogenicity) and anomalies at maternal exposures less than the human exposure based on area under the curve (AUC) at the 450 mg daily clinical dose (see Data). Advise pregnant women of the potential risk to a fetus.

In the U.S. general population, the estimated background risk of major birth defects and miscarriage in clinically recognized pregnancies is 2% to 4% and 15% to 20%, respectively.

Data

Animal Data

In embryo-fetal development studies, pregnant rabbits received oral doses of 0.5, 5, 25, 50, 150, or 450 mg/kg tepotinib hydrochloride hydrate daily during organogenesis. Severe maternal toxicity occurred at the 450 mg/kg dose (approximately 0.75 times the human exposure at the 450 mg clinical dose). At 150 mg/kg (approximately 0.5 times the human exposure by AUC at the 450 mg clinical dose), two animals aborted and one animal died prematurely; mean fetal body weight was also decreased. A dose-dependent increase of skeletal malformations, including malrotations of fore and/or hind paws with concomitant misshapen scapula and/or malpositioned clavicle and/or calcaneus and/or talus, occurred at doses ≥ 5 mg/kg (approximately 0.003 times the human exposure by AUC at the 450 mg clinical dose); there was also an incidence of spina bifida at the 5 mg/kg dose level.

8.2 Lactation

Risk Summary

There are no data regarding the secretion of tepotinib or its metabolites in human milk or its effects on the breastfed infant or milk production. Advise women not to breastfeed during treatment with TEPMETKO and for one week after the last dose.

8.3 Females and Males of Reproductive Potential

Based on animal data, TEPMETKO can cause malformations at doses less than the human exposure based on AUC at the 450 mg clinical dose [see Use in Specific Populations (8.1)].

Pregnancy Testing

Verify pregnancy status in females of reproductive potential prior to initiating TEPMETKO [see Use in Specific Populations (8.1)].

Contraception

Females

Advise females of reproductive potential to use effective contraception during TEPMETKO treatment and for one week after the last dose.

Males

Advise male patients with female partners of reproductive potential to use effective contraception during TEPMETKO treatment and for one week after the last dose.

8.4 Pediatric Use

The safety and efficacy of TEPMETKO in pediatric patients have not been established.

8.5 Geriatric Use

Of 313 patients with NSCLC positive for METex14 skipping alterations in VISION who received 450 mg TEPMETKO once daily, 79% were 65 years or older, and 41% were 75 years or older. No clinically important differences in safety or efficacy were observed between patients aged 65 years or older and younger patients.

8.6 Renal Impairment

No dosage modification is recommended in patients with mild or moderate renal impairment (creatinine clearance [CLcr] 30 to 89 mL/min, estimated by Cockcroft-Gault). The recommended dosage has not been established for patients with severe renal impairment (CLcr < 30 mL/min) [see Clinical Pharmacology (12.3)].

8.7 Hepatic Impairment

No dosage modification is recommended in patients with mild (Child Pugh Class A) or moderate (Child Pugh Class B) hepatic impairment. The pharmacokinetics and safety of tepotinib in patients with severe hepatic impairment (Child Pugh Class C) have not been studied [see Clinical Pharmacology (12.3)].

11 DESCRIPTION

Tepotinib is a kinase inhibitor. TEPMETKO (tepotinib) tablets for oral use are formulated with tepotinib hydrochloride hydrate. The chemical name for tepotinib hydrochloride hydrate is 3-{1-[(3-{5-[(1-methylpiperidin-4-yl)methoxy]pyrimidin-2-yl}phenyl)methyl]-6-oxo-1,6-dihydropyridazin-3-yl}benzonitrile hydrochloride hydrate. The molecular formula is C29H28N6O2∙HCl∙H2O and the molecular weight is 547.05 g/mol for tepotinib hydrochloride hydrate and 492.58 g/mol for tepotinib (free base). The chemical structure is shown below:

Tepotinib hydrochloride hydrate is a white to off-white powder with a pKa of 9.5.

TEPMETKO is supplied as film-coated tablets containing 225 mg of tepotinib (equivalent to 250 mg tepotinib hydrochloride hydrate). Inactive ingredients in the tablet core are mannitol, microcrystalline cellulose, crospovidone, magnesium stearate, and colloidal silicon dioxide. The tablet coating consists of hypromellose, titanium dioxide, lactose monohydrate, polyethylene glycol, triacetin, and red iron oxides.

12 CLINICAL PHARMACOLOGY

12.1 Mechanism of Action

Tepotinib is a kinase inhibitor that targets MET, including variants with exon 14 skipping alterations. Tepotinib inhibits hepatocyte growth factor (HGF)-dependent and -independent MET phosphorylation and MET-dependent downstream signaling pathways. Tepotinib also inhibited melatonin 2 and imidazoline 1 receptors at clinically achievable concentrations.

In vitro, tepotinib inhibited tumor cell proliferation, anchorage-independent growth, and migration of MET-dependent tumor cells. In mice implanted with tumor cell lines with oncogenic activation of MET, including METex14 skipping alterations, tepotinib inhibited tumor growth, led to sustained inhibition of MET phosphorylation, and, in one model, decreased the formation of metastases.

12.2 Pharmacodynamics

Exposure-Response

Tepotinib exposure-response relationships and the time course of pharmacodynamic response have not been fully characterized.

Cardiac Electrophysiology

At the recommended dosage, no large mean increases in QTc (i.e. > 20 ms) were detected in patients with various solid tumors. A concentration-dependent increase in QTc interval was observed. The QTc effect of tepotinib at high clinical exposures has not been evaluated.

12.3 Pharmacokinetics

The pharmacokinetics of tepotinib were evaluated in patients with cancer administered 450 mg once daily unless otherwise specified. Tepotinib exposure (AUC0-12h and Cmax) increases dose-proportionally over the dose range of 27 mg (0.06 times the recommended daily dosage) to 450 mg. At the recommended dosage, the geometric mean (coefficient of variation [CV] %) steady state Cmax was 1,291 ng/mL (48.1%) and the AUC0-24h was 27,438 ng∙h/mL (51.7%). The oral clearance of tepotinib did not change with respect to time. The median accumulation was 2.5-fold for Cmax and 3.3-fold for AUC0-24h after multiple daily doses of tepotinib.

Absorption

The median Tmax of tepotinib is 8 hours (range from 6 to 12 hours). The geometric mean (CV%) absolute bioavailability of TEPMETKO in the fed state was 71.6% (10.8%) in healthy subjects.

Effect of Food

The mean AUC0-INF of tepotinib increased by 1.6-fold and Cmax increased by 2-fold, following administration of a high-fat, high-calorie meal (approximately 800 to 1,000 calories, 150 calories from protein, 250 calories from carbohydrate, and 500 to 600 calories from fat). The median Tmax shifted from 12 hours to 8 hours.

Distribution

The geometric mean (CV%) apparent volume of distribution (VZ/F) of tepotinib is 1,038 L (24.3%). Protein binding of tepotinib is 98% and is independent of drug concentration at clinically relevant exposures.

Elimination

The apparent clearance (CL/F) of tepotinib is 23.8 L/h (87.5%) and the half-life is 32 hours following oral administration of TEPMETKO in patients with cancer.

Metabolism

Tepotinib is primarily metabolized by CYP3A4 and CYP2C8. One major circulating plasma metabolite (M506) has been identified.

Excretion

Following a single oral administration of a radiolabeled dose of 450 mg tepotinib, approximately 85% of the dose was recovered in feces (45% unchanged) and 13.6% in urine (7% unchanged). The major circulating metabolite M506 accounted for about 40.4% of the total radioactivity in plasma.

Specific Populations

No clinically significant effects on tepotinib pharmacokinetics were observed based on age (18 to 89 years), race/ethnicity (White, Black, Asian, Japanese, and Hispanic), sex, body weight (35.5 to 136 kg), mild to moderate renal impairment (CLcr 30 to 89 mL/min), or mild to moderate hepatic impairment (Child-Pugh A and B). The effect of severe renal impairment (CLcr < 30 mL/min) and severe hepatic impairment (Child-Pugh C) on the pharmacokinetics of tepotinib has not been studied.

Drug Interaction Studies

Clinical Studies and Model-Informed Approaches

No clinically significant differences in the pharmacokinetics of tepotinib were observed when coadministered with the following drugs: itraconazole (strong CYP3A and P-gp inhibitor), carbamazepine (strong CYP3A inducer) or omeprazole (proton pump inhibitor/acid reducing agent) under fed conditions.

No clinically significant differences in the pharmacokinetics of the following drugs were observed or predicted when coadministered with tepotinib: midazolam (sensitive CYP3A substrate) or CYP2C9 substrates.

P-gp Substrates: Coadministration of TEPMETKO with dabigatran etexilate (P-gp substrate) increased dabigatran Cmax by 40% and AUC0-INF by 50%.

MATE2 and OCT2 Substrates: No clinically relevant differences in glucose levels were observed when metformin (MATE2 and OCT2 substrate) was coadministered with tepotinib.

In Vitro Studies

Cytochrome P450 Enzymes: Tepotinib is a substrate of CYP3A4 and CYP2C8. Tepotinib and M506 do not inhibit CYP1A2, CYP2A6, CYP2B6, CYP2C8, CYP2C19, CYP2D6 or CYP2E1, and do not induce CYP1A2 or 2B6 at clinically relevant concentrations.

UDP-Glucuronosyltransferase (UGT): Tepotinib and M506 do not inhibit UGT 1A1, 1A9, 2B17, 1A3/4/6 and 2B7/15 at clinically relevant concentrations.

Transporter Systems: Tepotinib is a P-gp substrate. Tepotinib may inhibit intestinal BCRP at clinically relevant concentrations. Tepotinib does not inhibit bile salt export pump (BSEP), organic anion transporter polypeptide (OATP) 1B1, B3, or organic anion transporter (OAT) 1 and 3.

13 NONCLINICAL TOXICOLOGY

13.1 Carcinogenesis, Mutagenesis, Impairment of Fertility

Carcinogenicity studies have not been performed with tepotinib. Tepotinib and its major circulating metabolite were not mutagenic in vitro in the bacterial reverse mutation (Ames) assay, or a mouse lymphoma assay. In vivo, tepotinib was not genotoxic in a rat micronucleus test.

Fertility studies of tepotinib have not been performed. There were no morphological changes in male or female reproductive organs in repeat-dose toxicity studies in dogs.

14 CLINICAL STUDIES

The efficacy of TEPMETKO was evaluated in a single-arm, open-label, multicenter, non-randomized, multicohort study (VISION, NCT02864992). Eligible patients were required to have advanced or metastatic NSCLC harboring METex14 skipping alterations, epidermal growth factor receptor (EGFR) wild-type and anaplastic lymphoma kinase (ALK) negative status, at least one measurable lesion as defined by Response Evaluation Criteria in Solid Tumors (RECIST) version 1.1, and Eastern Cooperative Oncology Group (ECOG) Performance Status of 0 to 1. Patients with symptomatic CNS metastases, clinically significant uncontrolled cardiac disease, or who received treatment with any MET or hepatocyte growth factor (HGF) inhibitor were not eligible for the study.

Identification of METex14 skipping alterations was prospectively determined using central laboratories employing either a PCR-based or next-generation sequencing-based clinical trial assay using tissue (66%) and/or plasma (57%) samples.

Patients received TEPMETKO 450 mg once daily until disease progression or unacceptable toxicity. The major efficacy outcome measure was confirmed overall response rate (ORR) according to Response Evaluation Criteria in Solid Tumors (RECIST v1.1) as evaluated by a Blinded Independent Review Committee (BIRC). An additional efficacy outcome measure was duration of response (DOR) by BIRC.

The efficacy population included 164 treatment naïve patients and 149 previously treated patients. The median age was 72 years (range 41 to 94 years); 51% female; 62% White, 34% Asian; 26% had Eastern Cooperative Oncology Group (ECOG) Performance Status (PS) 0 and 74% had ECOG PS 1; 49% never smoked; 81% had adenocarcinoma; 94% had metastatic disease; and 13% had CNS metastases. Amongst previously treated patients, 84% received prior platinum-based chemotherapy.

Efficacy results are presented in Table 4.

Table 4: Efficacy Results in the VISION study
Efficacy parameter | Treatment-Naïve (N=164) | Previously Treated (N=149)
Overall response rate (95% CI) [Blinded Independent Review Committee (BIRC) review.] , [Confirmed responses.] | 57% (49, 65) | 45% (37, 53)
Duration of Response
Range in months [Based on observed duration of response.] | 1.3+, 56.6+ | 1.4+, 67.6+
Patients with DOR ≥ 6 months | 66% | 66%
Patients with DOR ≥ 12 months | 40% | 36%
CI: Confidence interval, + denotes ongoing response.

16 HOW SUPPLIED/STORAGE AND HANDLING

TEPMETKO (tepotinib) tablets: 225 mg tepotinib, white-pink, oval, biconvex film-coated tablet with embossment "M" on one side and plain on the other side.

NDC number | Size
44087-5000-3 | Box of 30 tablets: 3 blister cards each containing 10 tablets
44087-5000-6 | Box of 60 tablets: 6 blister cards each containing 10 tablets

The blister cards consist of a child-resistant blister foil.

STORAGE AND HANDLING

Store TEPMETKO at 20°C-25°C (68°F-77°F); excursions permitted to 15°C-30°C (59°F-86°F) [see USP-NF Controlled Room Temperature]. Store in original package.

17 PATIENT COUNSELING INFORMATION

Advise the patient to read the FDA-approved patient labeling (Patient Information).

Interstitial Lung Disease (ILD)/Pneumonitis

Inform patients of the risk of severe or fatal ILD/pneumonitis. Advise patients to contact their healthcare provider immediately to report new or worsening respiratory symptoms [see Warnings and Precautions (5.1)].

Hepatotoxicity

Inform patients that they will need to undergo lab tests to monitor liver function. Advise patients to immediately contact their healthcare provider for signs and symptoms of liver dysfunction [see Warnings and Precautions (5.2)].

Pancreatic Toxicity

Inform patients that they will need to undergo lab tests to monitor pancreatic function. Advise patients to immediately contact their healthcare provider for signs and symptoms of pancreatitis [see Warnings and Precautions (5.3)].

Embryo-Fetal Toxicity

Advise males and females of reproductive potential that TEPMETKO can cause fetal harm.

Advise females of reproductive potential to use effective contraception during and for one week after the last dose of TEPMETKO [see Warnings and Precautions (5.4) and Use in Specific Populations (8.3)].

Advise male patients with female partners of reproductive potential to use effective contraception during treatment with TEPMETKO and for one week after the last dose of TEPMETKO [see Warnings and Precautions (5.4) and Use in Specific Populations (8.3)].

Lactation

Advise women not to breastfeed during treatment with TEPMETKO and for one week after the last dose [see Use in Specific Populations (8.2)].

Drug Interactions

Advise patients to inform their healthcare provider of all concomitant medications, including prescription medicines, over-the-counter drugs and herbal products [see Drug Interactions (7)].

Dosing and Administration

Instruct patients to take 450 mg TEPMETKO once daily with food [see Dosage and Administration (2.2)].

Missed Dose

Advise patients that a missed dose of TEPMETKO can be taken as soon as remembered on the same day, unless the next dose is due within 8 hours. If vomiting occurs after taking a dose of TEPMETKO, advise patients to take the next dose at the scheduled time [see Dosage and Administration (2.2)].

Manufactured for:

EMD Serono, Inc.
Boston, MA 02210
U.S.A.

TEPMETKO is a trademark of Merck KGaA,
Darmstadt, Germany

PATIENT INFORMATION
TEPMETKO® (tep-MET-co)
(tepotinib)
tablets, for oral use

What is the most important information I should know about TEPMETKO?
TEPMETKO may cause serious side effects, including:

- Lung problems. TEPMETKO may cause severe or life-threatening swelling (inflammation) of the lungs during treatment that can lead to death. Tell your healthcare provider right away if you develop any new or worsening symptoms of lung problems, including:
  - trouble breathing
  - shortness of breath
  - cough
  - fever

See "What are possible side effects of TEPMETKO?" for more information about side effects.

What is TEPMETKO?
TEPMETKO is a prescription medicine used to treat adults with non-small cell lung cancer (NSCLC) that:

- has spread to other parts of the body (metastatic), and
- whose tumors have an abnormal mesenchymal epithelial transition (MET) gene. Your healthcare provider will perform a test to make sure that TEPMETKO is right for you.

It is not known if TEPMETKO is safe and effective in children.

Before you take TEPMETKO, tell your healthcare provider about all of your medical conditions, including if you:

- have or have had lung or breathing problems other than your lung cancer
- have or have had liver problems
- have or have had pancreatic problems
- are pregnant or plan to become pregnant. TEPMETKO can harm your unborn baby.
  Females who are able to become pregnant:
  - Your healthcare provider may do a pregnancy test before you start treatment with TEPMETKO.
  - You should use effective birth control (contraception) during treatment and for 1 week after the last dose of TEPMETKO. Talk to your healthcare provider about birth control methods that may be right for you.
  Males with female partners who are able to become pregnant should use effective birth control (contraception) during treatment with TEPMETKO and for 1 week after the last dose of TEPMETKO.
- are breastfeeding or plan to breastfeed. It is not known if TEPMETKO passes into your breast milk. Do not breastfeed during treatment and for 1 week after the last dose of TEPMETKO.

Tell your healthcare provider about all the medicines you take, including prescription and over-the-counter medicines, vitamins, and herbal supplements.

How should I take TEPMETKO?

- Take TEPMETKO exactly as your healthcare provider tells you to. Do not change your dose or stop taking TEPMETKO unless your healthcare provider tells you to.
- Take TEPMETKO 1 time a day with food.
- Take your dose of TEPMETKO at about the same time each day.
- Swallow TEPMETKO tablets whole. Do not chew, crush or split the tablets.
  If you cannot swallow TEPMETKO tablets whole:
  - Place your prescribed dose of TEPMETKO tablets in a glass that contains 30 mL (1 ounce) of non-carbonated water. Do not use or add any other liquids.
  - Stir the TEPMETKO tablets and water until the TEPMETKO tablets are in small pieces (the tablets will not completely dissolve). Do not crush TEPMETKO tablets.
  - Drink the TEPMETKO and water mixture right away or within 1 hour. Make sure to swallow the mixture. Do not chew pieces of the tablet.
  - Add another 30 mL of non-carbonated water to the glass and drink it right away to get your full dose of TEPMETKO.
  If you have a nasogastric (NG) tube that is 8 French gauge or larger:
  - Follow the same instructions for mixing TEPMETKO tablets in a glass that contains 30 mL of non-carbonated water.
  - Do not use or add any other liquids.
  - Stir the TEPMETKO tablets and water until the TEPMETKO tablets are in small pieces (the tablets will not completely dissolve). Do not crush TEPMETKO tablets.
  - Give the TEPMETKO tablet and water mixture using the NG tube manufacturer instructions right away or within 1 hour.
  - Pieces of the tablet may remain in the glass. Right away, add 30 mL of non-carbonated water into the glass. Give the water and any remaining TEPMETKO through the NG tube right away to make sure that all of the medicine is given. Repeat this step. This will help to ensure that no medicine is left in the glass or syringe and the full prescribed dose of TEPMETKO is given.
- If you miss a dose of TEPMETKO, take it as soon as you remember. If your next dose is due within 8 hours, skip the missed dose and take your next dose at your regular scheduled time.
- If you vomit after taking a dose of TEPMETKO, take your next dose at your regular scheduled time.

What are the possible side effects of TEPMETKO?
TEPMETKO may cause serious side effects, including:

- See "What is the most important information I should know about TEPMETKO?"
- Liver problems. TEPMETKO may cause abnormal liver blood test results. Your healthcare provider will do blood tests to check your liver function before you start treatment and during treatment with TEPMETKO. Tell your healthcare provider right away if you develop any signs and symptoms of liver problems, including:

- your skin or the white part of your eyes turns yellow
- dark or "tea colored" urine
- light-colored stools (bowel movements)
- confusion
- tiredness
- loss of appetite for several days or longer

- nausea and vomiting
- pain, aching, or tenderness on the right side of your stomach-area (abdomen)
- weakness
- swelling in your stomach-area

- Pancreas problems. TEPMETKO may cause increases in your blood amylase and lipase levels that may indicate a problem with your pancreas. Your healthcare provider will do blood tests to check your pancreatic function before you start treatment and during treatment with TEPMETKO. Tell your healthcare provider right away if you develop any signs and symptoms of pancreas problems, including:

- upper stomach (abdominal) pain that may spread to your back and get worse with eating
- weight loss

- nausea
- vomiting

The most common side effects of TEPMETKO include:

- swelling in your face or other parts of your body
- nausea
- tiredness
- muscle and joint pain
- diarrhea

- shortness of breath
- rash
- changes in certain blood tests

Your healthcare provider may change your dose, temporarily stop, or permanently stop treatment with TEPMETKO if you develop serious side effects during treatment.
These are not all of the possible side effects of TEPMETKO.
Call your doctor for medical advice about side effects. You may report side effects to FDA at 1-800-FDA-1088.

How should I store TEPMETKO?

- Store TEPMETKO at room temperature between 68°F to 77°F (20°C to 25°C).
- TEPMETKO tablets come in blister cards with a child-resistant blister foil.
- Store TEPMETKO in original package.

Keep TEPMETKO and all medicines out of the reach of children.

General information about the safe and effective use of TEPMETKO.
Medicines are sometimes prescribed for purposes other than those listed in a Patient Information leaflet. Do not use TEPMETKO for a condition for which it was not prescribed. Do not give TEPMETKO to other people, even if they have the same symptoms you have. It may harm them. You can ask your pharmacist or healthcare provider for information about TEPMETKO that is written for health professionals.

What are the ingredients in TEPMETKO?
Active ingredient: tepotinib
Inactive ingredients: mannitol, microcrystalline cellulose, crospovidone, magnesium stearate, and colloidal silicon dioxide.
Tablet coating: hypromellose, titanium dioxide, lactose monohydrate, polyethylene glycol, triacetin, and red iron oxides.
Manufactured for: EMD Serono, Inc., Boston, MA 02210, U.S.A.
TEPMETKO is a trademark of Merck KGaA, Darmstadt, Germany.
Product of Germany.
For more information, call toll-free 1-844-662-3631 or go to www.TEPMETKO.com.

This Patient Information has been approved by the U.S. Food and Drug Administration.

Revised 01/2025

PRINCIPAL DISPLAY PANEL - 30 Tablet Blister Pack Carton

NDC 44087-5000-3

TEPMETKO®
(tepotinib) tablets
225 mg per tablet

Rx Only

Each tablet contains 225 mg of tepotinib
(equivalent to 250 mg tepotinib hydrochloride hydrate)

Each carton contains 3 child resistant blister
cards of 10 tablets each

30 tablets

EMD
SERONO

PRINCIPAL DISPLAY PANEL - 60 Tablet Blister Pack Carton

NDC 44087-5000-6

TEPMETKO®
(tepotinib) tablets
225 mg per tablet

Rx Only

Each tablet contains 225 mg of tepotinib
(equivalent to 250 mg tepotinib hydrochloride hydrate)

Each carton contains 6 child resistant blister
cards of 10 tablets each

60 tablets

EMD
SERONO